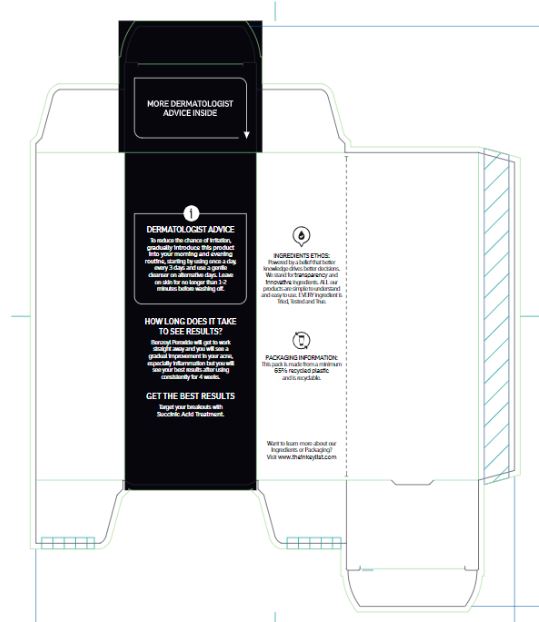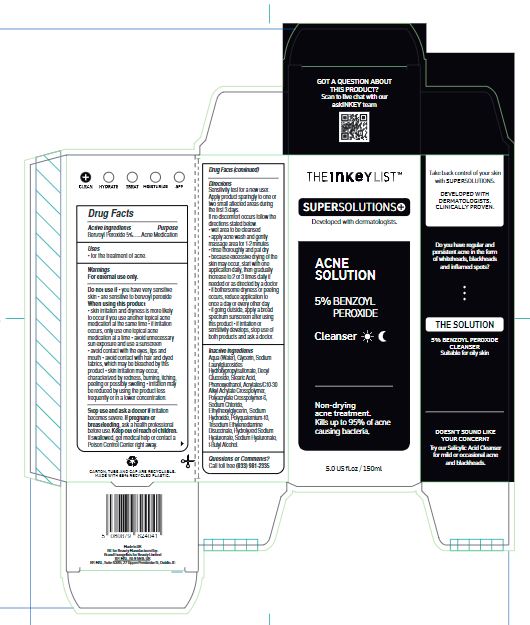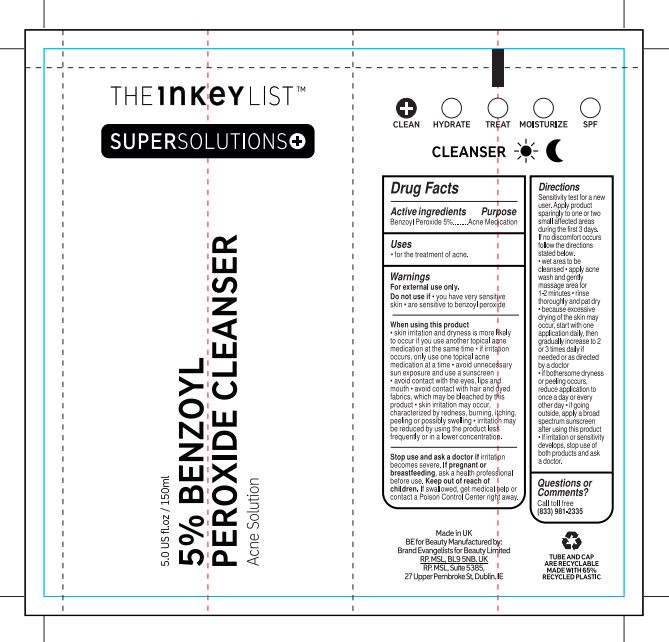 DRUG LABEL: 5 Percent Benzoyl Peroxide Cleanser
NDC: 81136-023 | Form: GEL
Manufacturer: Brand Evangelists for Beauty Limited
Category: otc | Type: HUMAN OTC DRUG LABEL
Date: 20231110

ACTIVE INGREDIENTS: BENZOYL PEROXIDE 50 mg/1 mL
INACTIVE INGREDIENTS: WATER; GLYCERIN; SODIUM LAUROYL HYDROXYPROPYL SULFONATE; DECYL GLUCOSIDE; STEARIC ACID; PHENOXYETHANOL; CARBOMER INTERPOLYMER TYPE B (ALLYL PENTAERYTHRITOL CROSSLINKED); AMMONIUM ACRYLOYLDIMETHYLTAURATE, DIMETHYLACRYLAMIDE, LAURYL METHACRYLATE AND LAURETH-4 METHACRYLATE COPOLYMER, TRIMETHYLOLPROPANE TRIACRYLATE CROSSLINKED (45000 MPA.S); SODIUM CHLORIDE; ETHYLHEXYLGLYCERIN; SODIUM HYDROXIDE; TRISODIUM ETHYLENEDIAMINE DISUCCINATE; HYALURONATE SODIUM; TERT-BUTYL ALCOHOL

5 Percent Benzoyl Peroxide Cleanser

Active ingredients

Benzoyl Peroxide 5%

Purpose

Acne Medication

Uses

• for the treatment of acne.

Warnings

For external use only.

Do not use if

• you have very sensitive skin• are sensitive to benzoyl peroxide

When using this product

• skin irritation and dryness is more likely to occur if you use another topical acne medication at the same time • if irritation occurs, only use one topical acne medication at a time • avoid unnecessary sun exposure and use a sunscreen • avoid contact with the eyes, lips and mouth • avoid contact with hair and dyed fabrics, which may be bleached by this product • skin irritation may occur, characterized by redness, burning, itching, peeling or possibly swelling • irritation may be reduced by using the product less frequently or in a lower concentration.

Stop use and ask a doctor if

irritation becomes severe.

If pregnant or breastfeeding

ask a health professional before use.

Keep out of reach of children.

If swallowed, get medical help or contact a Poison Control Center right away.

Directions

Sensitivity test for a new user. Apply product sparingly to one or two small affected areas during the first 3 days. If no discomfort occurs follow the directions stated below.• wet area to be cleansed • apply acne wash and gently massage area for 1-2 minutes • rinse thoroughly and pat dry • because excessive drying of the skin may occur, start with one application daily, then gradually increase to 2 or 3 times daily if needed or as directed by a doctor • if bothersome dryness or peeling occurs, reduce application to once a day or every other day • if going outside, apply a broad spectrum sunscreen after using this product • if irritation or sensitivity develops, stop use of both products and ask a doctor.

Inactive ingredients

Aqua (Water), Glycerin, Sodium Laurylglucosides Hydroxypropylsulfonate, Decyl Glucoside, Stearic Acid, Phenoxyethanol, Acrylates/C10-30 Alkyl Acrylate Crosspolymer, Polyacrylate Crosspolymer-6, Sodium Chloride, Ethylhexylglycerin, SodiumHydroxide, Polyquaternium-10, Trisodium Ethylenediamine Disuccinate, Hydrolyzed Sodium Hyaluronate, Sodium Hyaluronate, t-Butyl Alcohol.

Questions or Comments?

Call toll free (833) 981-2335